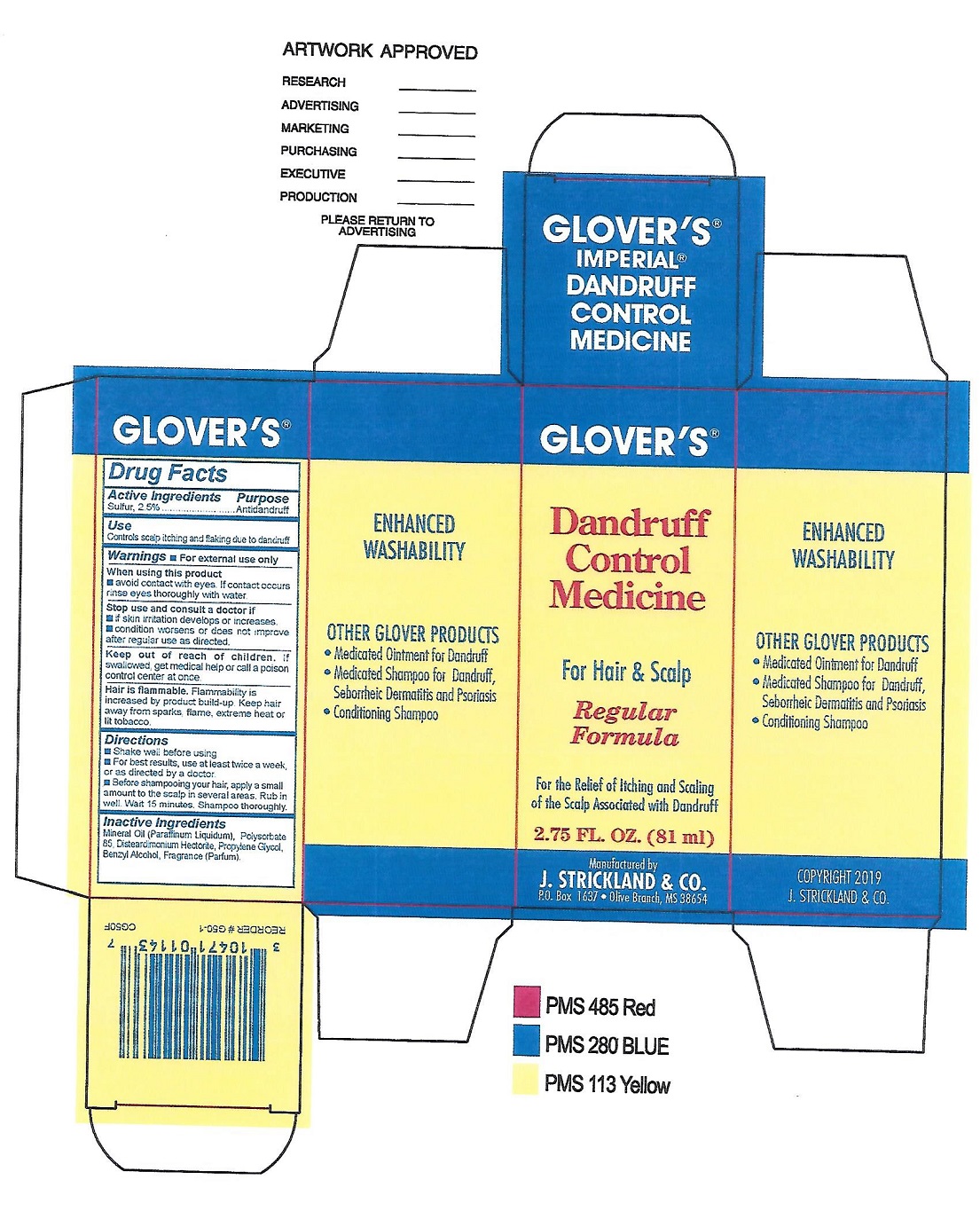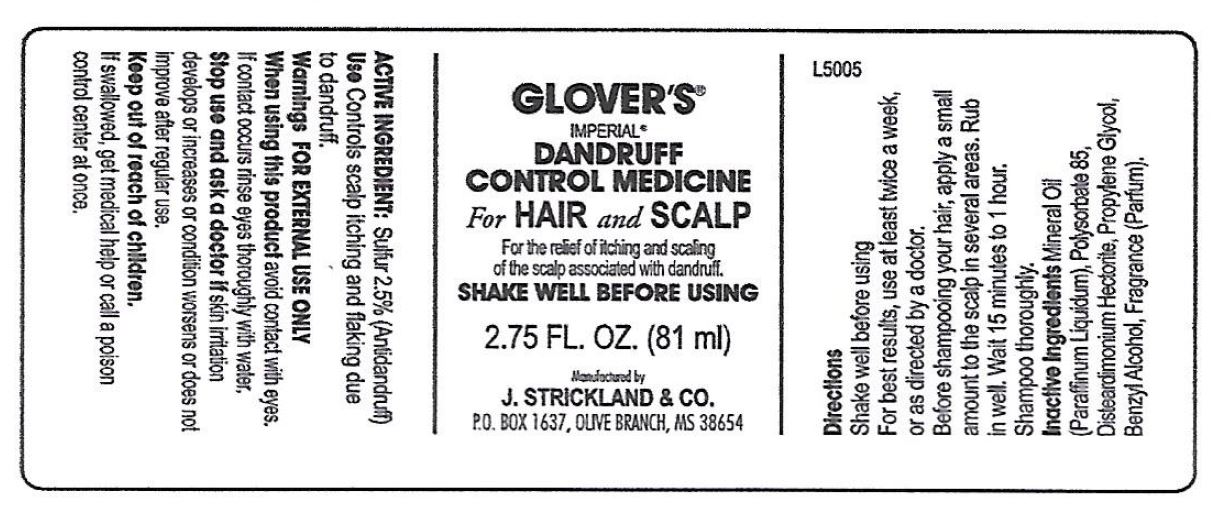 DRUG LABEL: Glovers Dandruff Control Medicine, Regular
NDC: 12022-007 | Form: SUSPENSION
Manufacturer: J. Strickland & Co.
Category: otc | Type: HUMAN OTC DRUG LABEL
Date: 20231021

ACTIVE INGREDIENTS: SULFUR 25 mg/1 mL
INACTIVE INGREDIENTS: MINERAL OIL; POLYSORBATE 85; DISTEARDIMONIUM HECTORITE; PROPYLENE GLYCOL; BENZYL ALCOHOL

Glover's Dandruff Control Medicine, Regular

Active Ingredients:

Sulfur, 2.5%

Purpose

Antidandruff

Uses:

Controls scalp itching and flaking due to dandruff

Warnings:

For External Use Only.

When using this product

- do not get into eyes. If contact occurs rinse eyes thoroughly with water.

Stop use and consult a doctor if

- if skin irritation develops or increases.
- condition worsens or does not improve after regular use.

Keep out of reach of children

If swallowed, get medical help or call a poison control center at once.

Directions:

- Shake well before using.
- For best results, use at leats twice a week, or as directed by a doctor.
- Before shampooimg your hair, apply a small amount to the scalp in several areas. Rub in well. Wait 15 minutes to 1 hour Shampoo thoroughly

Inactive Ingredients:

Mineral Oil (Paraffum Liquidum), Polysorbate-85, Disteardimonium Hectorite, Propylene Glycol, Benzyl Alcohol, Fragrance (Parfum).